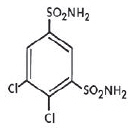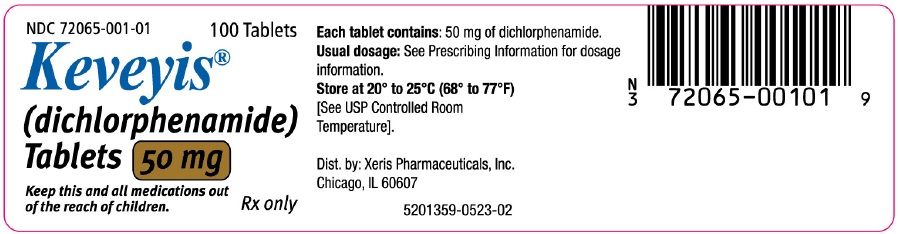 DRUG LABEL: Keveyis
NDC: 72065-001 | Form: TABLET
Manufacturer: Xeris Pharmaceuticals, Inc.
Category: prescription | Type: HUMAN PRESCRIPTION DRUG LABEL
Date: 20251223

ACTIVE INGREDIENTS: DICHLORPHENAMIDE 50 mg/1 1
INACTIVE INGREDIENTS: LACTOSE MONOHYDRATE; MAGNESIUM STEARATE; STARCH, CORN

HIGHLIGHTS OF PRESCRIBING INFORMATION

These highlights do not include all the information needed to use KEVEYIS® safely and effectively. See full prescribing information for KEVEYIS®.
KEVEYIS® (dichlorphenamide) tablets, for oral use
Initial U.S. Approval: 1958

1 INDICATIONS AND USAGE

KEVEYIS is an oral carbonic anhydrase inhibitor indicated for the treatment of primary hyperkalemic periodic paralysis, primary hypokalemic periodic paralysis, and related variants (1)

2 DOSAGE AND ADMINISTRATION

- Initiate dosing at 50 mg by mouth once or twice daily (2.1)
- Titrate up or down dose based on individual response (2.1)
- The minimum recommended dosage is 50 mg daily, and the maximum recommended dosage is 200 mg daily (2.1)
- Evaluate response to KEVEYIS after 2 months of treatment (2.2)

3 DOSAGE FORMS AND STRENGTHS

Tablets: 50 mg (3)

4 CONTRAINDICATIONS

- Hepatic insufficiency (4)
- Severe pulmonary obstruction (4)
- Hypersensitivity to dichlorphenamide or other sulfonamides (4)
- Concomitant use with high dose aspirin (4)

5 WARNINGS AND PRECAUTIONS

- Hypersensitivity and Other Life-Threatening Reactions: discontinue KEVEYIS at the first appearance of skin rash or any sign of immune-mediated or idiosyncratic adverse reaction (5.1)
- Hypokalemia: baseline and periodic measurements of serum potassium are recommended; if hypokalemia develops or persists, consider reducing the dose or discontinuing KEVEYIS and correcting potassium levels (5.3)
- Metabolic acidosis: baseline and periodic measurements of serum bicarbonate are recommended; if metabolic acidosis develops or persists, consider reducing the dose or discontinuing KEVEYIS (5.4)
- Falls: consider reducing the dose or discontinuing KEVEYIS in patients who experience falls (5.5)

6 ADVERSE REACTIONS

Most common adverse reactions (incidence at least 10% and greater than placebo) include paresthesias, cognitive disorder, dysgeusia, and confusional state (6.1)

To report SUSPECTED ADVERSE REACTIONS, contact Xeris Pharmaceuticals, Inc. at 1-855-324-8912, or FDA at 1-800-FDA-1088 or www.fda.gov/medwatch.

7 DRUG INTERACTIONS

Aspirin: anorexia, tachypnea, lethargy, and coma have been reported with concomitant use of dichlorphenamide and high-dose aspirin. The concomitant use of KEVEYIS and high-dose aspirin is contraindicated. KEVEYIS should be used with caution in patients receiving lower doses of aspirin (4, 5.2, 7.1)

8 USE IN SPECIFIC POPULATIONS

Pregnancy: Based on animal data, may cause fetal harm (8.1)

FULL PRESCRIBING INFORMATION

1 INDICATIONS AND USAGE

KEVEYIS is indicated for the treatment of primary hyperkalemic periodic paralysis, primary hypokalemic periodic paralysis, and related variants.

2 DOSAGE AND ADMINISTRATION

2.1 Dosage Information

Initiate dosing at 50 mg by mouth once or twice daily. The dosage may be increased or decreased based on individual response, at weekly intervals (or sooner in case of adverse reaction). The minimum recommended total daily dosage is 50 mg, and the maximum recommended total daily dosage is 200 mg.

2.2 Monitoring to Assess Effectiveness

Primary hyperkalemic periodic paralysis, primary hypokalemic periodic paralysis, and related variants are a heterogeneous group of conditions, for which the response to KEVEYIS may vary. Therefore, prescribers should evaluate the patient's response to KEVEYIS after 2 months of treatment to decide whether KEVEYIS should be continued.

2.3 Monitoring to Assess Safety

Baseline and periodic measurements of serum potassium and serum bicarbonate during KEVEYIS treatment is recommended [see Warnings and Precautions (5.3, 5.4)].

3 DOSAGE FORMS AND STRENGTHS

Round, white tablets, scored on one side, engraved with "D" above the score and "50" below the score, the other side is plain, 50 mg each.

4 CONTRAINDICATIONS

KEVEYIS is contraindicated in the following circumstances:

- Hypersensitivity to dichlorphenamide or other sulfonamides [see Warnings and Precautions (5.1)]
- Concomitant use of KEVEYIS and high dose aspirin [see Warnings and Precautions (5.2) and Drug Interactions (7.1)]
- Severe pulmonary disease, limiting compensation to metabolic acidosis caused by KEVEYIS [see Warnings and Precautions (5.4)]
- Hepatic insufficiency: KEVEYIS may aggravate hepatic encephalopathy.

5 WARNINGS AND PRECAUTIONS

5.1 Hypersensitivity and Other Life-Threatening Reactions

Fatalities associated with the administration of sulfonamides have occurred because of adverse reactions including Stevens-Johnson syndrome, toxic epidermal necrolysis, fulminant hepatic necrosis, agranulocytosis, aplastic anemia and other blood dyscrasias. Pulmonary involvement can occur in isolation or as part of a systemic reaction.

KEVEYIS should be discontinued at the first appearance of skin rash or any sign of immune-mediated or other life-threatening adverse reaction.

5.2 Concomitant Use of Aspirin or Other Salicylates

Carbonic anhydrase inhibitors, including KEVEYIS, can cause metabolic acidosis [see Warnings and Precautions (5.4)] , which can increase the risk of salicylate toxicity. Anorexia, tachypnea, lethargy, and coma have been reported with concomitant use of dichlorphenamide and high-dose aspirin. Therefore, the concomitant use of KEVEYIS and high-dose aspirin is contraindicated. Patients with concomitant use of KEVEYIS and low-dose aspirin should be carefully monitored.

5.3 Hypokalemia

KEVEYIS increases potassium excretion and can cause hypokalemia. The risk of hypokalemia is greater when KEVEYIS is used in patients with conditions associated with hypokalemia (e.g., adrenocortical excess, renal tubular acidosis type 1 and 2), and in patients receiving other drugs that may cause hypokalemia [see Drug Interactions (7.3)] .

Baseline and periodic measurements of serum potassium during KEVEYIS treatment is recommended.

If hypokalemia develops or persists, consideration should be given to reducing the dose or discontinuing KEVEYIS and correction of potassium levels.

5.4 Metabolic Acidosis

KEVEYIS can cause hyperchloremic non-anion gap metabolic acidosis. Concomitant use of KEVEYIS with other drugs that cause metabolic acidosis may increase the severity of acidosis. Concomitant use of KEVEYIS in compensated patients with respiratory acidosis, such as in advanced lung diseases, may lead to respiratory decompensation.

Baseline and periodic measurements of serum bicarbonate during KEVEYIS treatment are recommended.

If metabolic acidosis develops or persists, consideration should be given to reducing the dose or discontinuing KEVEYIS [see Drug Interactions (7.4)] .

5.5 Falls

KEVEYIS increases the risk of falls. The risk of falls is greater in the elderly and with higher doses of KEVEYIS. Consider dose reduction or discontinuation of KEVEYIS in patients who experience falls while treated with KEVEYIS.

6 ADVERSE REACTIONS

The following serious adverse reactions are described elsewhere in labeling:

- Hypersensitivity and Other Life-Threatening Reactions [see Warnings and Precautions (5.1)]
- Hypokalemia [see Warnings and Precautions (5.3)]
- Metabolic Acidosis [see Warnings and Precautions (5.4)]
- Falls [see Warnings and Precautions (5.5)]

6.1 Clinical Trials Experience

Because clinical trials are conducted under widely varying conditions, adverse reaction rates observed in the clinical trials of a drug cannot be directly compared to rates in the clinical trials of another drug and may not reflect the rates observed in practice.

In a 9-week randomized controlled trial in adults with hyperkalemic or hypokalemic periodic paralysis (Study 1), the most common adverse reactions in patients treated with KEVEYIS, with rates greater than placebo, were paresthesia, cognitive disorder, dysgeusia, and confusional state. The mean dose of KEVEYIS was 94 mg/day in patients with hypokalemic periodic paralysis and 82 mg/day in patients with hyperkalemic periodic paralysis.

Table 1 lists the incidence of adverse reactions that occurred in ≥ 5% of patients treated with KEVEYIS and more commonly than in patients treated with placebo in Study 1.

Table 1: Adverse Reactions in Patients Treated with KEVEYIS with Incidence ≥ 5% and more common than in Patients Treated with Placebo in Study 1
 | Adverse Reaction | KEVEYIS N = 36 (%) | Placebo N = 29 (%)
Nervous system disorders | Paresthesia | 44 | 14
Nervous system disorders | Cognitive disorder [Cognitive disorder combined cases with the preferred terms of cognitive disorder, disturbance in attention, and mental impairment.] | 14 | 7
Nervous system disorders | Dysgeusia | 14 | 0
Nervous system disorders | Confusional state | 11 | 0
Nervous system disorders | Headache | 8 | 7
Nervous system disorders | Hypoesthesia | 8 | 0
Nervous system disorders | Lethargy | 8 | 0
Nervous system disorders | Dizziness | 6 | 0
Gastrointestinal disorders | Diarrhea | 6 | 3
Gastrointestinal disorders | Nausea | 6 | 0
General disorders and administration site conditions | Fatigue | 8 | 0
General disorders and administration site conditions | Malaise | 6 | 0
Investigations | Weight decreased | 6 | 0
Musculoskeletal and connective tissue disorders | Muscle spasms | 8 | 0
Musculoskeletal and connective tissue disorders | Arthralgia | 6 | 3
Musculoskeletal and connective tissue disorders | Muscle twitching | 6 | 0
Respiratory | Dyspnea | 6 | 0
Respiratory | Pharyngolaryngeal pain | 6 | 0
Skin | Rash | 8 | 0
Skin | Pruritus | 6 | 0

6.2 Postmarketing Experience

Adverse reactions have been identified during postapproval use of dichlorphenamide. Because these reactions are reported voluntarily from a population of uncertain size, it is not always possible to reliably estimate their frequency or establish a causal relationship to drug exposure.

The following are adverse reactions which have been reported during postapproval use of dichlorphenamide and were serious or are not reported in the previous section of labeling [see Clinical Trials Experience (6.1)] : amnesia, cardiac failure, condition aggravated, convulsion, hallucination, nephrolithiasis, pancytopenia, psychotic disorder, renal tubular necrosis, stupor, syncope, tremor.

7 DRUG INTERACTIONS

7.1 Aspirin and Other Salicylates

Carbonic anhydrase inhibitors, including KEVEYIS, can cause metabolic acidosis [see Warnings and Precautions (5.2, 5.4)], which can increase the risk of salicylate toxicity. Anorexia, tachypnea, lethargy, and coma have been reported with concomitant use of dichlorphenamide and high-dose aspirin. Therefore, concomitant use of KEVEYIS and high-dose aspirin is contraindicated. Patients with concomitant use of KEVEYIS and low-dose aspirin should be carefully monitored [see Contraindications (4) and Warnings and Precautions (5.2)].

7.2 Drugs that are Substrates of Organic Anion Transporter1 (OAT1)

In vitro, dichlorphenamide is an inhibitor of OAT1 transporters. The concomitant administration of KEVEYIS may increase the plasma exposures of OAT1 substrates. Use of KEVEYIS with drugs that are sensitive to OAT1 inhibition (e.g., methotrexate, famotidine, oseltamivir) is not recommended [see Clinical Pharmacology (12.3)].

7.3 Drugs that Cause Hypokalemia

The risk of hypokalemia is greater with coadministration of KEVEYIS and other drugs that can cause hypokalemia (e.g., loop diuretics, thiazide diuretics, laxatives, antifungals, penicillins, and theophylline) [see Warnings and Precautions (5.3)] .

7.4 Drugs that Cause Metabolic Acidosis

Coadministration of KEVEYIS and other drugs that can cause metabolic acidosis may increase the severity of the acidosis [see Warnings and Precautions (5.4)].

7.5 Drugs that are Inhibitors of OAT1 or OAT3

An in vitro transporter study indicated that dichlorphenamide is a substrate of human transporters OAT1 and OAT3 [see Clinical Pharmacology (12.3)] . Therefore, signs of dichlorphenamide toxicity should be monitored when administered with OAT1 or OAT3 inhibitors.

8 USE IN SPECIFIC POPULATIONS

8.1 Pregnancy

Risk Summary
There are no adequate data on the developmental risk associated with the use of KEVEYIS in pregnant women. A no-effect dose has not been established. Dichlorphenamide was teratogenic when administered orally to pregnant rats.

The background risk of major birth defects and miscarriage for the indicated population is unknown. In the U.S. general population, the estimated background risk of major birth defects and miscarriage in clinically recognized pregnancies is 2% to 4%, and 15% to 20%, respectively.

Clinical Considerations
Fetal/Neonatal adverse reactions
KEVEYIS treatment can cause metabolic acidosis [see Warnings and Precautions (5.4)]. The effect of dichlorphenamide-induced metabolic acidosis has not been studied in pregnancy; however, metabolic acidosis in pregnancy (due to other causes) can cause decreased fetal growth, decreased fetal oxygenation, and fetal death, and may affect the fetus’ ability to tolerate labor. Pregnant patients should be monitored for metabolic acidosis and treated as in the nonpregnant state. Newborns of mothers treated with KEVEYIS should be monitored for metabolic acidosis because of possible occurrence of transient metabolic acidosis following birth.

Labor or Delivery
Although the effect of KEVEYIS on labor and delivery in humans has not been established, the development of dichlorphenamide-induced metabolic acidosis in the mother and/or in the fetus might affect the fetus’ ability to tolerate labor.

Data
Animal Data
Teratogenic effects (fetal limb reduction defects) were reported following oral administration of dichlorphenamide to pregnant rats during organogenesis at 350 mg/kg, or 17 times the maximum recommended human dose (200 mg/day) on a body surface area (mg/m ^2) basis. A no-effect dose for adverse effects on embryofetal development has not been established.

8.2 Lactation

Risk Summary
There are no data on the presence of dichlorphenamide in human milk, the effects on the breastfed infant, or the effects on milk production.

The developmental and health benefits of breastfeeding should be considered along with the mother’s clinical need for KEVEYIS and any potential adverse effects on the breastfed infant from KEVEYIS or from the underlying maternal condition.

8.4 Pediatric Use

Safety and effectiveness of KEVEYIS in pediatric patients have not been established.

8.5 Geriatric Use

The risk of falls and of metabolic acidosis are greater in elderly patients [see Warnings and Precautions (5.4, 5.5)] .

10 OVERDOSAGE

Symptoms of overdosage or toxicity may include drowsiness, anorexia, nausea, vomiting, dizziness, ataxia, tremor, and tinnitus.

In the event of overdosage, induce emesis or perform gastric lavage. The electrolyte disturbances most likely to be encountered from overdosage are hypokalemia and hyperchloremic metabolic acidosis.

11 DESCRIPTION

KEVEYIS tablets contain dichlorphenamide, an oral carbonic anhydrase inhibitor. Dichlorphenamide, a dichlorinated benzenedisulfonamide, is known chemically as 4, 5–dichloro-1,3-benzenedisulfonamide.

Its empirical formula is C 6H 6Cl 2N 2O 4S 2 and its structural formula is:

Dichlorphenamide USP is a white or practically white, crystalline compound with a molecular weight of 305.16. It is very slightly soluble in water but soluble in dilute solutions of sodium carbonate and sodium hydroxide. Dilute alkaline solutions of dichlorphenamide are stable at room temperature.

KEVEYIS (dichlorphenamide) tablets are supplied as tablets, for oral administration, each containing 50 mg dichlorphenamide. Inactive ingredients are lactose monohydrate, magnesium stearate and pregelatinized starch.

12 CLINICAL PHARMACOLOGY

12.1 Mechanism of Action

Dichlorphenamide is a carbonic anhydrase inhibitor. However, the precise mechanism by which dichlorphenamide exerts its therapeutic effects in patients with primary periodic paralysis is unknown.

12.2 Pharmacodynamics

KEVEYIS can cause metabolic acidosis, which can increase the risk of salicylate toxicity with coadministration [see Warnings and Precautions (5.2)]. KEVEYIS-induced metabolic acidosis can also increase in severity with coadministration of other drugs that cause metabolic acidosis [see Warnings and Precautions (5.4)].

12.3 Pharmacokinetics

After single-dose administration in healthy subjects in fasted state, dichlorphenamide Cmax and AUC increased in a dose-proportional manner within the range of 25 mg to 400 mg (2 times the maximum recommended dose). The steady-state is expected to be achieved within 10 days of twice-daily dosing.

Absorption
The median time to reach maximum concentration (Tmax) of dichlorphenamide was about 1.5 to 3 hours postdose after both single and multiple dose administrations.

Distribution
The plasma protein binding of dichlorphenamide is approximately 88%.

Elimination
Following a single-dose administration, mean terminal half-life was in the range of 32 to 66 hours.

Metabolism
Dichlorphenamide is not a substrate for CYP1A2, CYP2B6, CYP2C8, CYP2C9, CYP2C19, CYP2D6 and CYP3A4 isoforms when tested in vitro.

Drug Interaction Studies

In vitro Assessment of Drug Interactions

Drug-Metabolizing Enzyme Inhibition
Dichlorphenamide is not an inhibitor for CYP1A2, 2B6, 2C8, 2C9, 2C19, 2D6, or 3A4 enzymes when tested in vitro.

Drug-Metabolizing Enzyme Induction
Dichlorphenamide is not an inducer for CYP1A2, 2B6, or 3A4 enzymes when tested in vitro.

In vitro Assessment of Transporter-Drug Interactions
Dichlorphenamide is neither a substrate nor inhibitor for p-gp, BCRP, OATP1B1, OATP1B3, OAT2, OAT4, OCT1, OCT2, MATE1, or MATE2-K when tested in vitro.

Dichlorphenamide is not an inhibitor of OAT3, but is an inhibitor of OAT1 based on in vitro studies [see Drug Interactions (7.4)].

Dichlorphenamide is a substrate for transporters OAT1 and OAT3 based on in vitro studies [see Drug Interactions (7.2)] .

In Vivo Drug Interactions
The use of dichlorphenamide in combination with high-dose aspirin is contraindicated as it may lead to salicylate toxicity. The mechanism(s) of this interaction is not known.

Specific Populations
Geriatrics
The pharmacokinetics of dichlorphenamide in the elderly has not been determined.

13 NONCLINICAL TOXICOLOGY

13.1 Carcinogenesis, Mutagenesis, Impairment of Fertility

Carcinogenesis

Studies to assess the carcinogenic potential of dichlorphenamide have not been conducted.

Mutagenesis

Studies to assess the genotoxicity of dichlorphenamide have not been conducted.

Impairment of Fertility

Studies to assess the effects of dichlorphenamide on fertility have not been conducted.

14 CLINICAL STUDIES

The efficacy of KEVEYIS was evaluated in two clinical studies, Study 1 and Study 2.

Study 1

Study 1 was a 9-week, double blind, placebo-controlled multi-center study. Study 1 consisted of two substudies: a substudy in patients with hypokalemic periodic paralysis (n=44), and a substudy in patients with hyperkalemic periodic paralysis (n=21). The primary efficacy endpoint in both substudies was the average number of self-reported attacks of muscle weakness per week over the final 8 weeks of the trial. Withdrawal from the study for acute severe worsening (increase in attack frequency or severity) was also assessed as an endpoint.

In Study 1, the dose of KEVEYIS was 50 mg b.i.d. for treatment-naïve patients. Patients already on dichlorphenamide prior to the study continued on the same dose while on KEVEYIS during the study. In patients taking acetazolamide prior to the study, the dose of KEVEYIS was set at 20% of the acetazolamide dose. Dose reduction for tolerability was permitted.

Hypokalemic Periodic Paralysis Substudy of Study 1

In the hypokalemic periodic paralysis substudy, median age of patients was 45 years and 73% of patients were male. Patients treated with KEVEYIS (n=24) had 2.2 fewer attacks per week than patients (n=20) treated with placebo (p=0.02). None of the patients randomized to KEVEYIS reached the endpoint of withdrawal from the study for acute worsening, vs. five patients randomized to placebo. The mean dose of KEVEYIS at Week 9 was 94 mg/day.

Hyperkalemic Periodic Paralysis Substudy of Study 1

In the Hyperkalemic Periodic Paralysis substudy, median age of patients was 43 years and 43% of patients were male. During the double-blind treatment period, patients treated with KEVEYIS (n=12) had 3.9 fewer attacks per week than patients (n=9) treated with placebo (p=0.08). None of the patients randomized to KEVEYIS reached the endpoint of withdrawal from the study for acute worsening, vs. two patients randomized to placebo. The mean dose of KEVEYIS at Week 9 was 82 mg/day.

Study 2

Study 2 was a 35-week, double blind, placebo-controlled, multi-center, two-period crossover study. Study 2 also consisted of two substudies: a substudy in patients with hypokalemic periodic paralysis (n=42), and a substudy in patients with hyperkalemic periodic paralysis (n=31), including patients with Paramyotonia Congenita. The primary endpoint in the hypokalemic periodic paralysis substudy was the incidence of acute intolerable worsening (based on attack frequency or severity) necessitating withdrawal. The primary endpoint in the hyperkalemic periodic paralysis substudy was the average number of self-reported attacks of muscle weakness per week. Dosing was determined similarly to Study 1.

Hypokalemic Periodic Paralysis Substudy of Study 2

The hypokalemic periodic paralysis substudy included patients with a mean age of 38 years; 79% of patients were male. Acute intolerable worsening was observed in 2 patients on KEVEYIS vs. 11 patients on placebo (p=0.02). The mean dose of KEVEYIS at the end of the study was 96 mg/day.

Hyperkalemic Periodic Paralysis Substudy of Study 2

The hyperkalemic periodic paralysis substudy included patients with a mean age of 37 years; and 79% of patients were male. Patients treated had 2.3 fewer attacks per week on KEVEYIS than on placebo (p=0.006). The mean dose of KEVEYIS at the end of the study was 73 mg/day.

16 HOW SUPPLIED/STORAGE AND HANDLING

Each KEVEYIS (dichlorphenamide) tablet, 50 mg is round, white, scored on one side, engraved with "D" above the score and "50" below the score. The other side is plain.
KEVEYIS (dichlorphenamide) tablets are supplied as follows:
Bottles of 100......................................NDC 72065-001-01

STORAGE AND HANDLING

Store at 20°C to 25°C (68°F to 77°F) [See USP Controlled Room Temperature].

17 PATIENT COUNSELING INFORMATION

Worsening of Symptoms
Advise patients to notify their physician if they experience acute worsening of symptoms of periodic paralysis.

Hypersensitivity and Other Life-Threatening Reactions
Inform patients that hypersensitivity and immune mediated reactions can occur with KEVEYIS, and could be fatal. Advise patients to discontinue KEVEYIS and notify their healthcare provider immediately if they develop a rash or signs and symptoms of anaphylaxis or other life-threatening reactions [see Warnings and Precautions (5.1)].

Drug Interactions
Instruct patients to notify their healthcare provider of all of the drugs and over-the-counter medications that they take and to not take aspirin or other salicylates without first discussing with their healthcare provider [see Drug Interactions (7.1, 7.2, 7.3, 7.4)].

Metabolic Acidosis
Instruct patients to contact their healthcare provider immediately if they develop possible manifestations of metabolic acidosis (e.g., fast breathing, fatigue/tiredness, loss of appetite, or irregular heart beat or palpitations) [see Warnings and Precautions (5.4)].

Falls
Inform patients that KEVEYIS can increase their risk of falls [see Warnings and Precautions (5.5)].

Cognitive Impairment
Advise patients to notify their healthcare provider if they experience symptoms of cognitive impairment including confusion and memory lapse [see Adverse Reactions (6.1)].

Driving and Operating Machinery
KEVEYIS may cause drowsiness/fatigue in some patients [see Adverse Reactions (6.1)] . Caution patients on the potential for impaired ability to drive and operate machinery.

Distributed by:
Xeris Pharmaceuticals, Inc.
W Fulton St., Suite 1300
Chicago, IL 60607

KEVEYIS® is a registered trademark licensed exclusively in the US to Xeris Pharmaceuticals, Inc., a subsidiary of Xeris Biopharma, Inc.

XERIS PHARMACEUTICALS® and its associated logo are trademarks of Xeris Pharmaceuticals, Inc.

Copyright © 2025 Xeris Pharmaceuticals, Inc. All rights reserved.

PRINCIPAL DISPLAY PANEL - 50 mg Tablet Bottle Label

NDC 72065-001-01
100 Tablets

Keveyis®
(dichlorphenamide)
Tablets 50 mg

Keep this and all medications out
of the reach of children.
Rx only